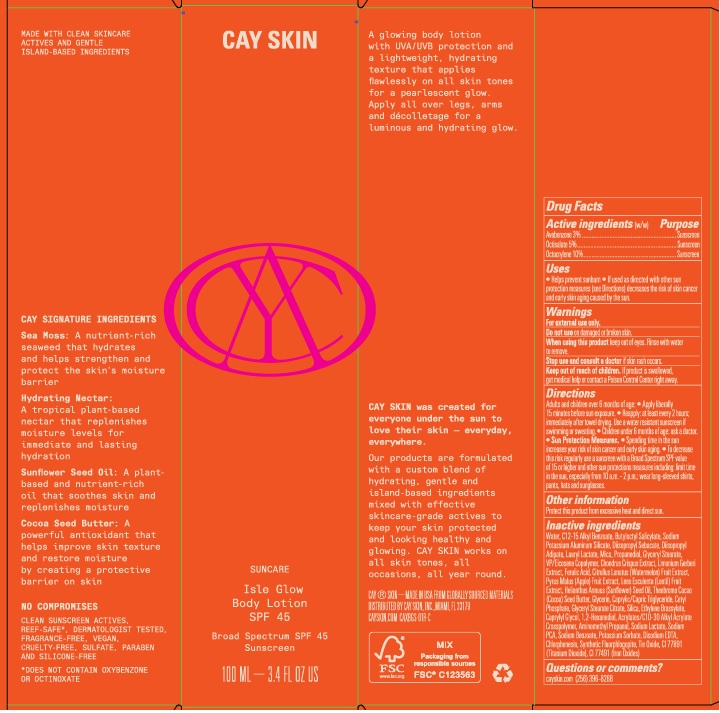 DRUG LABEL: Cay Skin Isle Glow Body SPF 45
NDC: 82657-003 | Form: LOTION
Manufacturer: Cay Skin, Inc.
Category: otc | Type: HUMAN OTC DRUG LABEL
Date: 20241205

ACTIVE INGREDIENTS: AVOBENZONE 30 mg/1 mL; OCTISALATE 50 mg/1 mL; OCTOCRYLENE 100 mg/1 mL
INACTIVE INGREDIENTS: ETHYLENE BRASSYLATE; MAGNESIUM POTASSIUM ALUMINOSILICATE FLUORIDE; EICOSYL POVIDONE; COCOA BUTTER; TITANIUM DIOXIDE; CHONDRUS CRISPUS; SUNFLOWER OIL; CETYL PHOSPHATE; SILICON DIOXIDE; CARBOMER INTERPOLYMER TYPE A (55000 CPS); CHLORPHENESIN; FERRIC OXIDE RED; 1,2-HEXANEDIOL; EDETATE DISODIUM ANHYDROUS; SODIUM LACTATE; POTASSIUM SORBATE; MEDIUM-CHAIN TRIGLYCERIDES; LIMONIUM GERBERI WHOLE; SODIUM PYRROLIDONE CARBOXYLATE; SODIUM BENZOATE; LAURYL LACTATE; GLYCERIN; WATER; BUTYLOCTYL SALICYLATE; DIISOPROPYL SEBACATE; DIISOPROPYL ADIPATE; MICA; PROPANEDIOL; APPLE; GLYCERYL STEARATE CITRATE; CAPRYLYL GLYCOL; AMINOMETHYLPROPANOL; GLYCERYL MONOSTEARATE; WATERMELON; LENTIL; FERULIC ACID; ALKYL (C12-15) BENZOATE; STANNOUS OXIDE

Cay Skin Isle Glow Body Lotion SPF 45

Active ingredients

Avobenzone 3%, Octisalate 5%, Octocrylene 10%

Purpose

Sunscreen

Uses

- Helps prevent sunburn
- If used as directed with other sun protection measures (see Directions) decreases the risk of skin cancer and early skin aging caused by the sun.

Warnings

For external use only.

Do not use

on damaged or broken skin.

When using this product

keep out of eyes. Rinse with water to remove.

Stop use and consult a doctor

if skin rash occurs.

Keep out of reach of children.

If product is swallowed, get medical help or contact a Poison Control Center right away.

Directions

- Adults and children over 6 months of age:
- Apply liberally 15 minutes before sun exposure.
- Reapply: at least every 2 hours; immediately after towel drying.
- Use a water resistant sunscreen if swimming or sweating.
- Children under 6 months of age: ask a doctor.
- Sun Protection Measures.
- Spending time in the sun increases your risk of skin cancer and early skin aging.
- To decrease this risk regularly use a sunscreen with a Broad Spectrum SPF value of 15 or higher and other sun protection measures including: limit time in the sun, especially from 10 a.m. - 2 p.m.; wear long-sleeved shirts, pants, hats and sunglasses.

Other information

Protect this product from excessive heat and direct sun.

Inactive ingredients

Water, C12-15 Alkyl Benzoate, Butyloctyl Salicylate, Sodium Potassium Aluminum Silicate, Diisopropyl Sebacate, Diisopropyl Adipate, Lauryl Lactate, Mica, Propanediol, Glyceryl Stearate, VP/Eicosene Copolylmer, Chondrus Crispus Extract, Limonium Gerberi Extract, Ferulic Acid, Citrullus Lanatus (Watermelon) Fruit Extract, Pyrus Malus (Apple) Fruit Extract, Lens Esculents (Lentil) Fruit Extract, Helianthus Annuus (Sunflower) Seed Oil, Theobroma Cacao (Cocoa) Seed Butter, Glycerin, Caprylic/Capric Triglyceride, Cetyl Phosphate, Glyceryl Stearate Citrate, Silica, Ethylene Brassylate, Caprylyl Glycol, 1,2-Hexanediol, Acrylates/C10-30 Alkyl Acrylate Crosspolymer, Aminomethyl Propanol, Sodium Lactate, Sodium PCA, Sodium Benzoate, Potassium Sorbate, Disodium EDTA, Chlorphenesin, Synthetic Fluorphlogopite, Tin Oxide, CI 77891 (Titanium Dioxide), CI 77491 (Iron Oxides)

Questions or comments?

cayskin.com (256) 396-8268